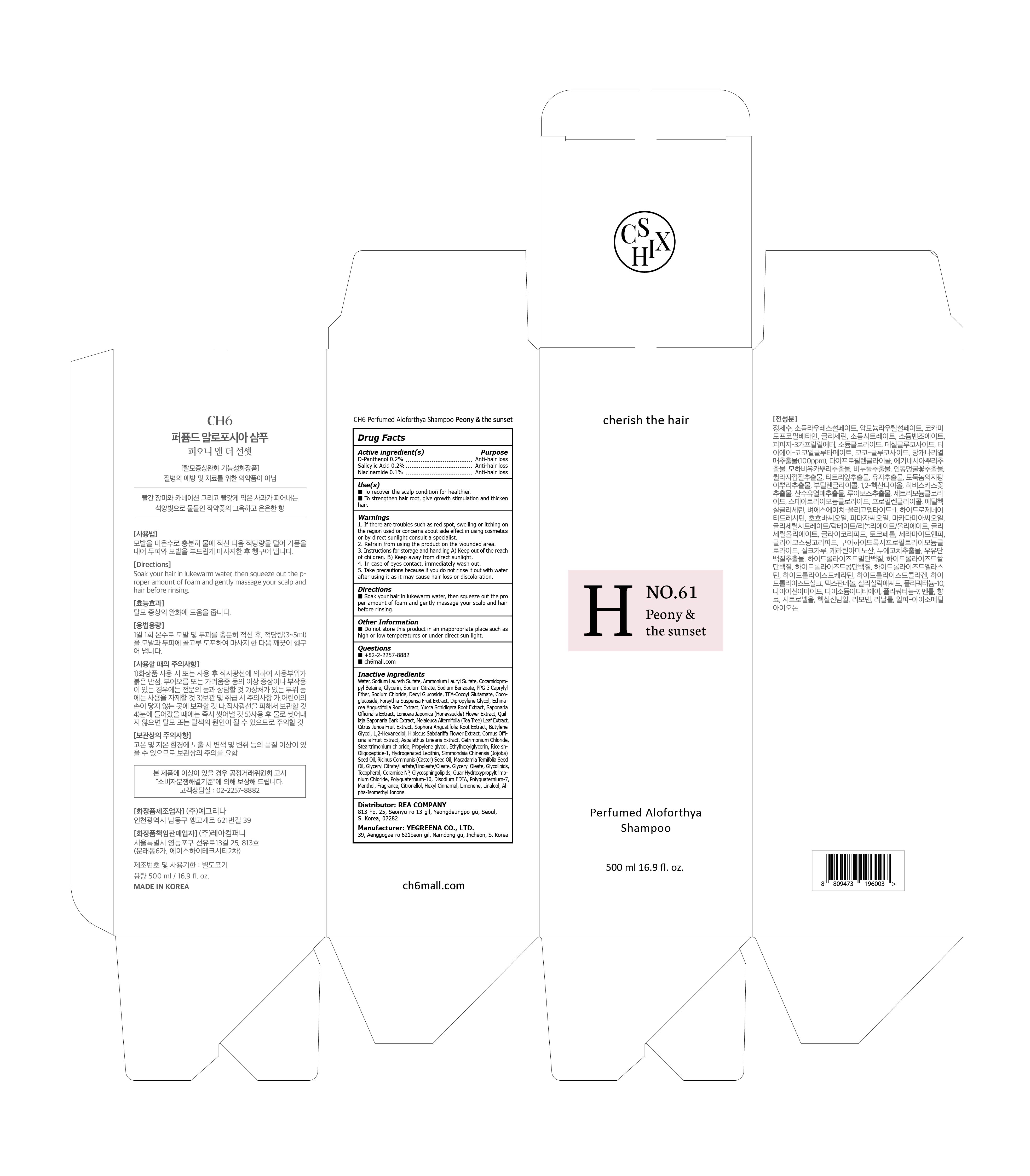 DRUG LABEL: CH6 Perfumed Aloforthya Peony and the sunset
NDC: 82916-050 | Form: SHAMPOO
Manufacturer: Rea Company
Category: otc | Type: HUMAN OTC DRUG LABEL
Date: 20220921

ACTIVE INGREDIENTS: DEXPANTHENOL 0.2 g/100 mL; SALICYLIC ACID 0.2 g/100 mL; NIACINAMIDE 0.1 g/100 mL
INACTIVE INGREDIENTS: Water; SODIUM LAURETH-3 SULFATE; AMMONIUM LAURYL SULFATE

ACTIVE INGREDIENTS

D-Panthenol 0.2%
Salicylic Acid 0.2%
Niacinamide 0.1%

PURPOSE

Anti-hair loss

Use(s)

■ To recover the scalp condition for healthier.
■ To strengthen hair root, give growth stimulation and thicken hair

Warnings

1. If there are troubles such as red spot, swelling or itching on the region used or concerns about side effect in using cosmetics or by direct sunlight consult a specialist.
2. Refrain from using the product on the wounded area.
3. Instructions for storage and handling A) Keep out of the reach of children.
B) Keep away from direct sunlight.
4. In case of eyes contact, immediately wash out.
5. Take precautions because if you do not rinse it out with water after using it as it may cause hair loss or discoloration.

KEEP OUT OF REACH OF CHILDREN

■ Keep out of reach of infants and children.

Directions

■ Soak your hair in lukewarm water, then squeeze out the proper amount of foam and gently massage your scalp and hair before rinsing .

Other Information

■ Do not store this product in an inappropriate place such as high or low temperatures or under direct sun light

Questions

■ +82-2-2257-8882
■ ch6mall.com

Inactive ingredients

Water, Sodium Laureth Sulfate, Ammonium Lauryl Sulfate, Cocamidopropyl Betaine, Glycerin, Sodium Citrate, Sodium Benzoate, PPG-3 Caprylyl Ether, Sodium Chloride, Decyl Glucoside, TEA-Cocoyl Glutamate, Coco-glucoside, Forsythia Suspensa Fruit Extract, Dipropylene Glycol, Echinacea Angustifolia Root Extract, Yucca Schidigera Root Extract, Saponaria Officinalis Extract, Lonicera Japonica (Honeysuckle) Flower Extract, Quillaja Saponaria Bark Extract, Melaleuca Alternifolia (Tea Tree) Leaf Extract, Citrus Junos Fruit Extract, Sophora Angustifolia Root Extract, Butylene Glycol, 1,2-Hexanediol, Hibiscus Sabdariffa Flower Extract, Cornus Officinalis Fruit Extract, Aspalathus Linearis Extract, Cetrimonium Chloride, Steartrimonium chloride, Propylene glycol, Ethylhexylglycerin, Rice sh-Oligopeptide-1, Hydrogenated Lecithin, Simmondsia Chinensis (Jojoba) Seed Oil, Ricinus Communis (Castor) Seed Oil, Macadamia Ternifolia Seed Oil, Glyceryl Citrate/Lactate/Linoleate/Oleate, Glyceryl Oleate, Glycolipids, Tocopherol, Ceramide NP, Glycosphingolipids, Guar Hydroxypropyltrimonium Chloride, Polyquaternium-10, Disodium EDTA, Polyquaternium-7, Fragrance, Citronellol, Hexyl Cinnamal, Limonene, Linalool, Alpha-Isomethyl Ionone